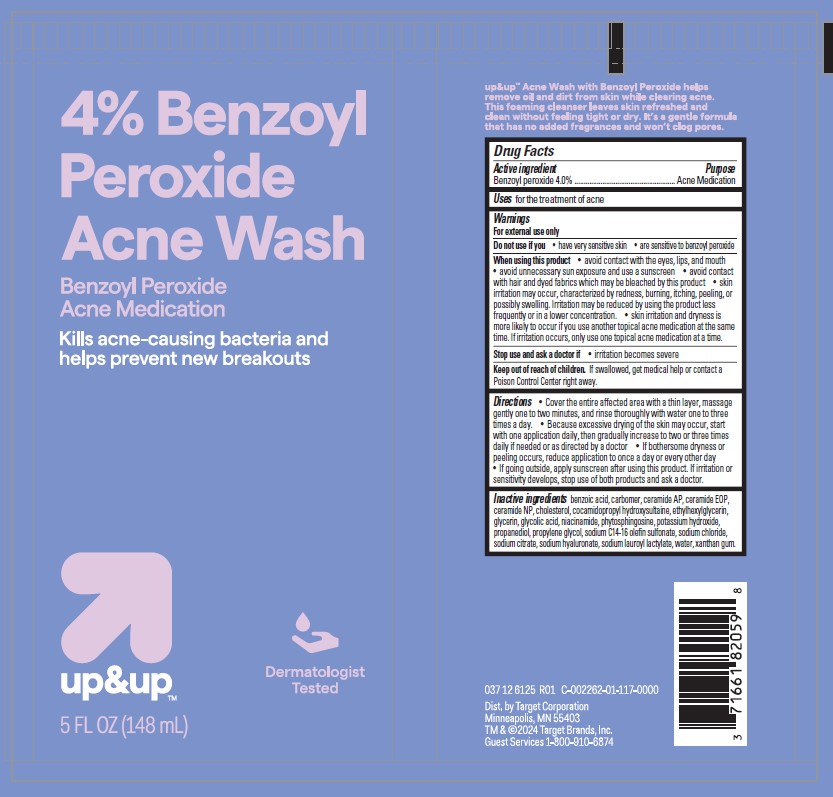 DRUG LABEL: Target Up and Up Benzoyl Peroxide Acne Wash
NDC: 82442-015 | Form: LIQUID
Manufacturer: TARGET CORPORATION
Category: otc | Type: HUMAN OTC DRUG LABEL
Date: 20240930

ACTIVE INGREDIENTS: BENZOYL PEROXIDE 40 mg/1 mL
INACTIVE INGREDIENTS: BENZOIC ACID; CERAMIDE AP; PHYTOSPHINGOSINE; CHOLESTEROL; WATER; GLYCERIN; PROPYLENE GLYCOL; COCAMIDOPROPYL HYDROXYSULTAINE; SODIUM C14-16 OLEFIN SULFONATE; XANTHAN GUM; POTASSIUM HYDROXIDE; SODIUM LAUROYL LACTYLATE; GLYCOLIC ACID; CERAMIDE NP; ETHYLHEXYLGLYCERIN; PROPANEDIOL; NIACINAMIDE; POLYACRYLIC ACID (250000 MW); HYALURONATE SODIUM; CARBOMER INTERPOLYMER TYPE A (ALLYL SUCROSE CROSSLINKED); SODIUM CHLORIDE; SODIUM CITRATE

Target Up and Up Benzoyl Peroxide Acne Wash

Active ingredient

Benzoyl peroxide 4.0%

Purpose

Acne Medication

Use

for the treatment of acne

Warnings

For external use only

Do not use

if you

• have very sensitive skin
• are sensitive to benzoyl peroxide

When using this product

- avoid contact with the eyes, lips, and mouth
- avoid unnecessary sun exposure and use a sunscreen
- avoid contact with hair and dyed fabrics, which may be bleached by this product
- skin irritation may occur, characterized by redness, burning, itching, peeling or possibly swelling. Irritation may be reduced by using the product less frequently or in a lower concentration.
- skin irritation and dryness is more likely to occur if you use another topical acne medication at the same time. If irritation occurs, only use one topical acne medication at a time.

Stop use and ask a doctor if

- skin irritation becomes severe

Keep out of reach of children.

If swallowed, get medical help or contact a Poison Control Center right away.

Directions

• Cover the entire affected area with a thin layer, massage
gently one to two minutes, and rinse thoroughly with water one to three
times a day. • Because excessive drying of the skin may occur, start
with one application daily, then gradually increase to two or three times
daily if needed or as directed by a doctor • If bothersome dryness or
peeling occurs, reduce application to once a day or every other day
• If going outside, apply sunscreen after using this product. If irritation or
sensitivity develops, stop use of both products and ask a doctor.

Inactive Ingredients

benzoic acid, carbomer, ceramide AP, ceramide EOP,
ceramide NP, cholesterol, cocamidopropyl hydroxysultaine, ethylhexylglycerin,
glycerin, glycolic acid, niacinamide, phytosphingosine, potassium hydroxide,
propanediol, propylene glycol, sodium C14-16 olefin sulfonate, sodium chloride,
sodium citrate, sodium hyaluronate, sodium lauroyl lactylate, water, xanthan gum.